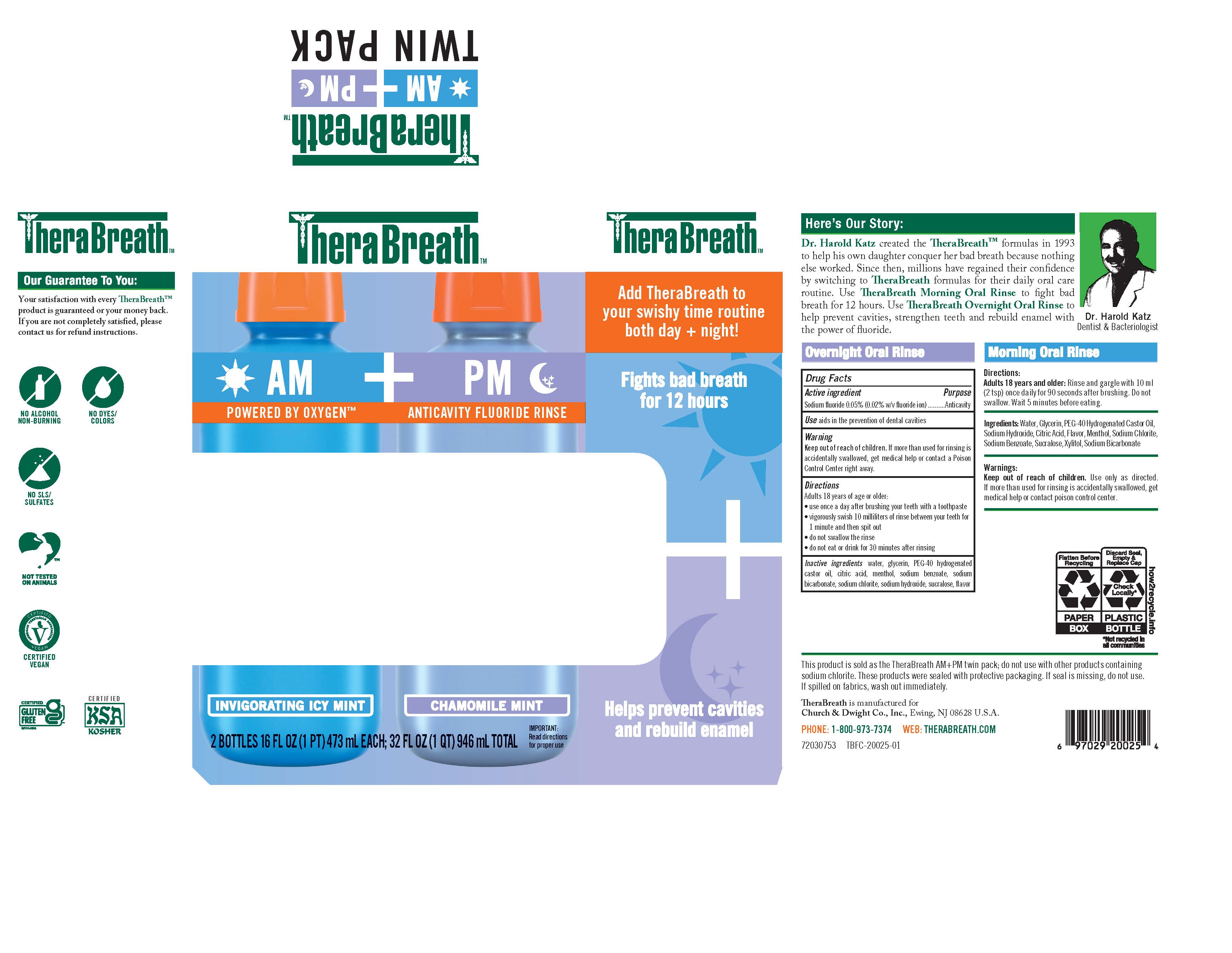 DRUG LABEL: TheraBreath
NDC: 10237-268 | Form: KIT | Route: ORAL
Manufacturer: Church & Dwight Co., Inc.
Category: otc | Type: HUMAN OTC DRUG LABEL
Date: 20251216

ACTIVE INGREDIENTS: SODIUM FLUORIDE 5 mg/10 mL
INACTIVE INGREDIENTS: WATER; GLYCERIN; SODIUM BENZOATE; SODIUM HYDROXIDE; SODIUM CHLORITE; CITRIC ACID MONOHYDRATE; SUCRALOSE; POLYOXYL 40 HYDROGENATED CASTOR OIL

Drug Facts

Overnight Oral Rinse

Active ingredient

Sodium fluoride 0.05% (0.02% w/v fluoride ion)

Purpose

Anticavity

Use

aids in the prevention of dental cavities

Warning

Keep out of reach of children. If more than used for rinsing is accidentally swallowed, get help or contact a Poison Control Center right away.

Directions

Adults 18 years of age or older:

- use once a day after brushing your teeth with a toothpaste
- vigorously swish 10 milliliters of rinse between your teeth for 1 minute and then spit out
- do not swallow the rinse
- do not eat or drink 30 minutes after rinsing

Inactive ingredients

water, glycerin, PEG-40 hyrogenated castor oil, citric acid, menthol, sodium benzoate, sodium bicarbonate, sodium chlorite, sodium hydroxide, sucralose, flavor

Principal Display Panel

TheraBreath AM + PM TWIN PACK

AM

POWERED BY OXYGENTM

INVIGORATING ICY MINT

PM

ANTICAVITY FLUORIDE RINSE

CHAMOMILE MINT

Helps prvent cavities and rebuild enamel

Add TheraBreath to your swishy time routine both day + night!

Fights bad breath for 12 hours